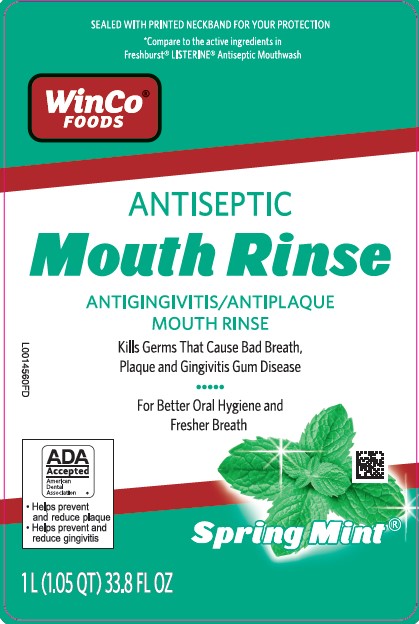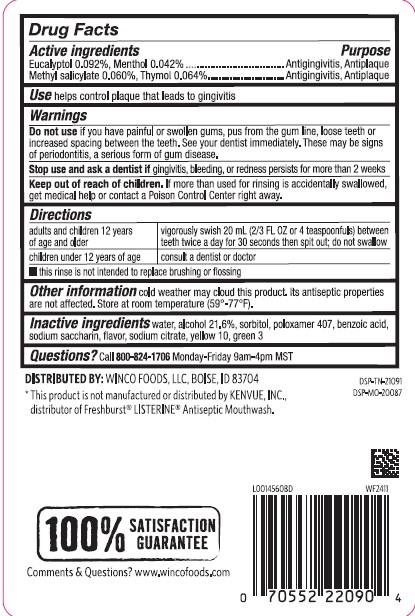 DRUG LABEL: Antiseptic
NDC: 67091-102 | Form: MOUTHWASH
Manufacturer: WinCo Foods, LLC
Category: otc | Type: HUMAN OTC DRUG LABEL
Date: 20260212

ACTIVE INGREDIENTS: EUCALYPTOL 0.92 mg/1 mL; MENTHOL 0.42 mg/1 mL; METHYL SALICYLATE 0.6 mg/1 mL; THYMOL 0.64 mg/1 mL
INACTIVE INGREDIENTS: WATER; ALCOHOL; SORBITOL; POLOXAMER 407; BENZOIC ACID; SACCHARIN SODIUM; SODIUM CITRATE; D&C YELLOW NO. 10; FD&C GREEN NO. 3

WinCo 072.003/072AL rev2-AN
Spring Mint Antiseptic Mouthrinse

Active ingredients

Eucalyptol 0.092%

Menthol 0.042%

Methyl salicylate 0.060%

Thymol 0.064%

Purpose

antigingivitis, antiplaque

Use

helps control plaque that leads to gingivitis

Warnings

for this product

Do not use

if you have painful or swollen gums, pus from the gum line, loose teeth or increased spacing between the teeth. See your dentist immediately. These may be signs of periodontitis, a serious form of gum disease.

Stop use and ask a dentist if

gingivitis, bleeding, or redness persists for more than 2 weeks

Keep out of reach of children

If more than used for rinsing is accidentally swallowed, get medical help or contact a Poison Control Center right away.

Directions

adults and children 12 years of age and older - vigorously swish 20 ml (2/3 FL OZ or 4 teaspoonfuls) between teeth twice a day for 30 seconds then spit out; do not swallow

children under 12 years of age - consult a dentist or doctor

- this rinse is not intended to replace brushing or flossing

Other information

cold weather may cloud this product. Its antiseptic properties are not affected. Store at room temperature (59° -77°F)

Inactive ingredients

water, alcohol 21.6%, sorbitol, poloxamer 407, benzoic acid, sodium saccharin, flavor, sodium citrate, yellow 10, green 3

Questions?

Call 800-824-1706 Monday - Friday 9am -4pm MST

Disclaimer

*This product is not manufactured or distributed by Kenvue, INC., distributor of Freshburst®LISTERINE®

Antiseptic Mouthwash.

Adverse reactions

DISTRIBUTED BY:WINCO FOODS, LLC BOISE, ID 83704

100% Satisfaction Guarantee

Comments & Questions? www.wincofoods.com

DSP-TN-21091

DSP-MO-20087

principal display panel

SEALED WITH PRINTED NECKBAND FOR YOUR PROTECTION

*Compare to the active ingredients in Freshburst®LISTERINE®Antiseptic Mouthwash

WinCo®

FOODS

ANTISEPTIC

MOUTH RINSE

ANTIGINGIVITIS/ANTIPLAQUE

MOUTH RINSE

Kills Germs That Cause Bad Breath, Plaque and Gingivitis Gum Disease

For Better Oral Hygiene and Fresher Breath

ADA Accepted

American Dental Association

- Helps prevent and reduce plaque
- Helps prevent and reduce gingivitis

Spring Mint®

1 L (1.05 QT) 33.8 FL OZ